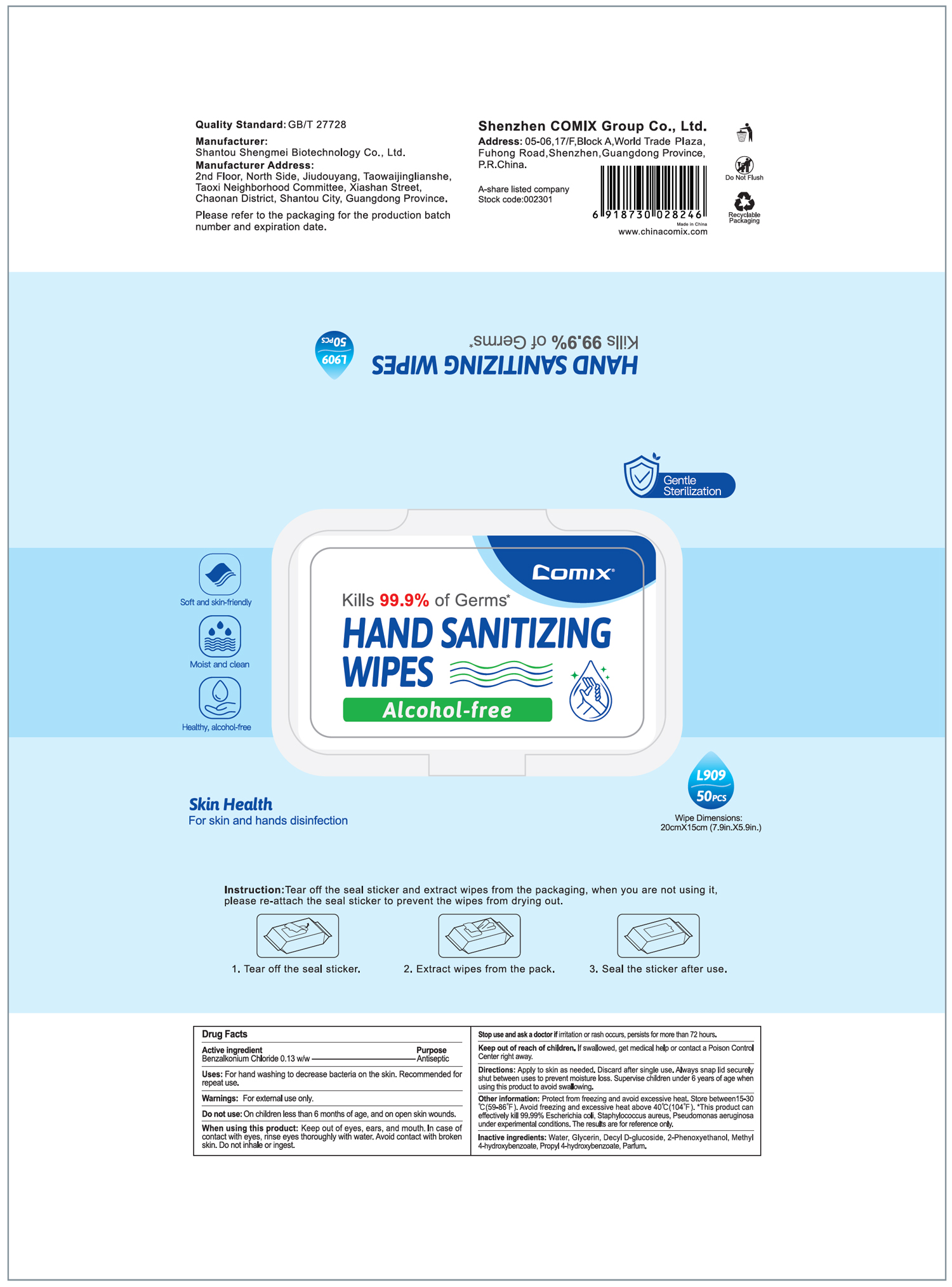 DRUG LABEL: Comix Hand Sanitizing Wipes
NDC: 55450-008 | Form: CLOTH
Manufacturer: Shantou Shengmei Biotechnology Co., Ltd.
Category: otc | Type: HUMAN OTC DRUG LABEL
Date: 20200820

ACTIVE INGREDIENTS: BENZALKONIUM CHLORIDE 0.13 g/100 g
INACTIVE INGREDIENTS: PHENOXYETHANOL; METHYLPARABEN; PROPYLPARABEN; GLYCERIN; DECYL GLUCOSIDE; WATER

Comix Hand Sanitizing Wipes

Active Ingredient

Benzalkonium Chloride 0.13% w/w. Purpose: Antiseptic

Purpose

Antiseptic, wipes

Uses

For hand washing to decrease bacteria on the skin. Recommended for repeat use.

Warnings

For external use only.

Do not use

on children less than 6 months of age, and on open skin wounds.

When using this product

Keep out of eyes, ears, and mouth. In case of contact with eyes, rinse eyes thoroughly with water. Avoid contact with broken skin. Do not inhale or ingest.

Stop use and ask doctor

if irritation or rash occurs, persists for more than 72 hours.

Keep out of reach of children.

If swallowed, get medical help or contact a Poison Control Center right away.

Directions

Apply to skin as needed. Discard after single use. Always snap lid securely shut between uses to prevent moisture loss. Supervise children under 6 years of age when using this product to avoid swallowing.

Other information

Protect from freezing and avoid excessive heat. Store between 15-30C (59-86F). Avoid freezing and excessive heat above 40C (104F). * This product can effectively kills 99.99% Escherichia coli, Staphylococcus aureus, Pseudomonas aeruginosa under experimental conditions. The results are for reference only.

Inactive ingredients

Water, Glycerin, Decyl D-glucoside, 2-Phenoxyethanol, Methyl 4-hydroxybenzoate, Propyl 4-hydroxybenzoate, Parfum

PACKAGE LABEL

55450-008-01 50PCS

Comix

Kills 99.99% of Germs*

HAND SANITIZING WIPES

Alcohol-free

Gentel Sterilization

Soft and skin friendly

Moisture and clean

Healthy, alcohol-free

L909

50 PCS

Wipe Dimensions

20cm X 15cm (7.9in X 5.9in)

Skin Health

For skin ad hands disinfection